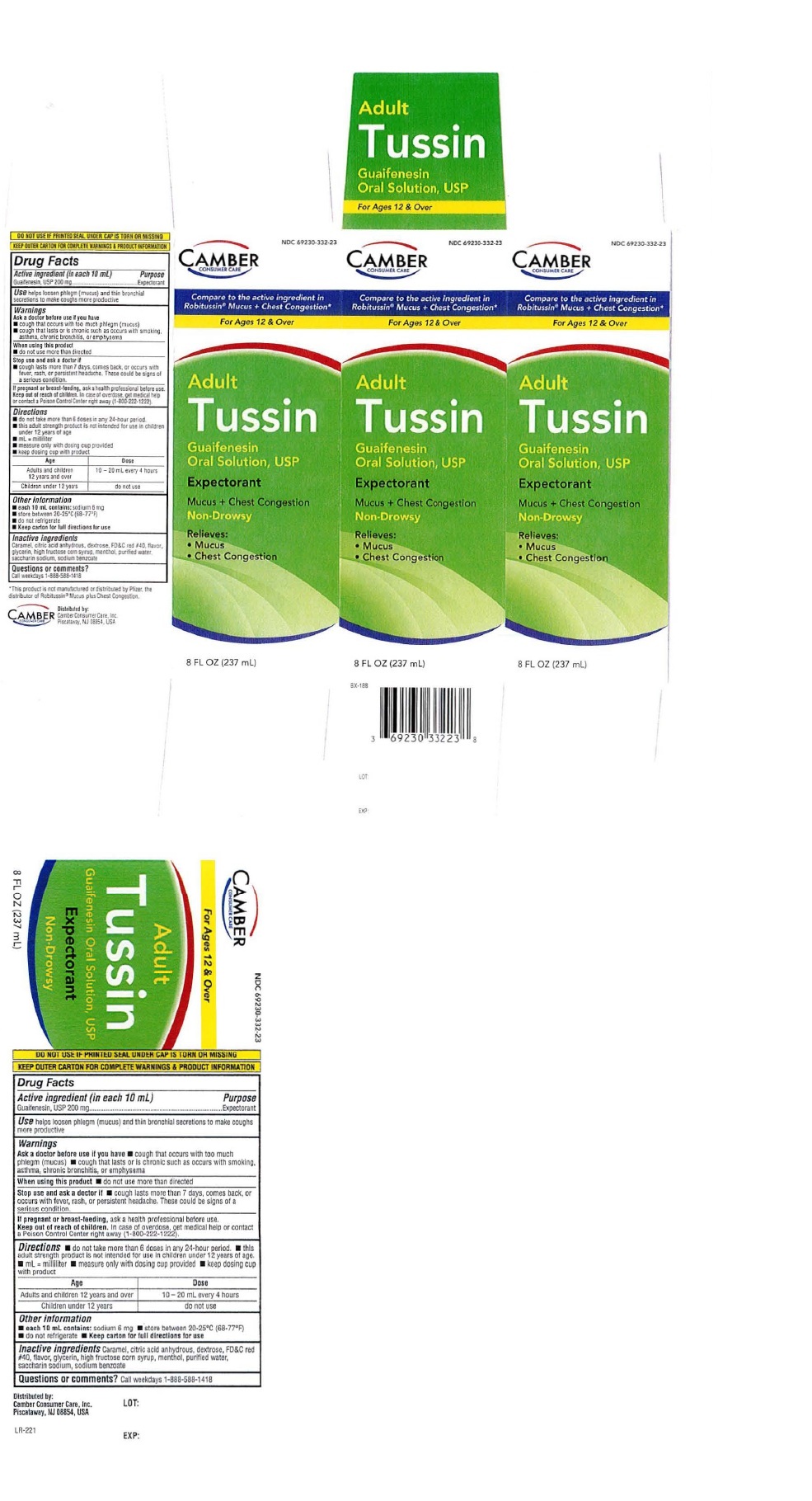 DRUG LABEL: Adult Tussin
NDC: 69230-332 | Form: SOLUTION
Manufacturer: Camber Consumer Care
Category: otc | Type: HUMAN OTC DRUG LABEL
Date: 20250520

ACTIVE INGREDIENTS: GUAIFENESIN 200 mg/10 mL
INACTIVE INGREDIENTS: CARAMEL; ANHYDROUS CITRIC ACID; DEXTROSE; FD&C RED NO. 40; GLYCERIN; HIGH FRUCTOSE CORN SYRUP; MENTHOL; WATER; SACCHARIN SODIUM; SODIUM BENZOATE

Adult Tussin Expectorant

Drug Facts

Active ingredients (in each 10 mL)

Guaifenesin, USP 200 mg

Purpose Expectorant

Uses
Helps loosen phlegm (mucus) and thin bronchial secretions to make coughs more productive

Warnings

Ask a doctor before use if you have
• cough that occurs with too much phlegm (mucus)
• cough that lasts or is chronic such as occurs with smoking, asthma, chronic bronchitis, or emphysema

When using this product
• do not use more than directed

Stop use and ask a doctor if
• cough lasts more than 7 days, comes back, or occurs with fever, rash, or persistent headache. These could be signs of a
serious condition.

If pregnant or breast-feeding, ask a health professional before use.

Keep out of reach of children. In case of overdose, get medical help or contact a Poison Control Center right away
(1-800-222-1222)

Directions
• do not take more than 6 doses in any 24-hour period • this adult strength product is not intended for use in children
under 12 years of age • ml = milliliter • measure only with dosing cup provided • keep dosing cup with product

Age Dose
Adults and Children 12 years and; over | 10-20 mL every 4 hours
Children under 12 years | Do not use

Other information
• each 10 mL contains: sodium 6 mg
• store between 20-25°C (68-77°F)
• do not refrigerate
• Keep carton for full directions for use.

Inactive ingredients
Caramel, citric acid anhydrous, dextrose, FD&C red # 40, flavor, glycerin, high fructose corn syrup, menthol, purified
water, saccharin sodium, sodium benzoate

QUESTIONS

Questions or comment? Call weekdays 1-888-588-1418

Package label: Adult Tussin Expectorant

Adult Tussin Expectorant

Guaifenesin Oral Solution, USP

8 FL OZ (237 mL)

DO NOT USE IF PRINTED SEAL UNDER CAP IS TORN OR MISSING
KEEP OUTER CARTON FOR COMPLETE WARNINGS & PRODUCT INFORMATION

Distributed by: LOT:

Camber Consumer Care Inc.
Piscataway, NJ 08854, U5A

EXP:

res